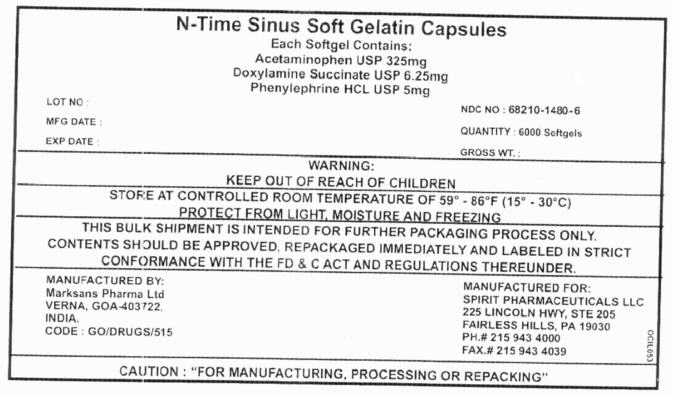 DRUG LABEL: N - TIME SINUS
NDC: 68210-1480 | Form: CAPSULE, LIQUID FILLED
Manufacturer: SPIRIT PHARMACEUTICALS,LLC
Category: otc | Type: HUMAN OTC DRUG LABEL
Date: 20100726

ACTIVE INGREDIENTS: ACETAMINOPHEN 325 mg/1 1; DOXYLAMINE SUCCINATE 6.25 mg/1 1; PHENYLEPHRINE Hydrochloride 5 mg/1 1
INACTIVE INGREDIENTS: POLYETHYLENE GLYCOL 400; PROPYLENE GLYCOL; GELATIN; POVIDONE; SORBITOL; WATER; GLYCERIN

N-Time Sinus Soft Gelatin Capsules

Drug Facts

ACTIVE INGREDIENT

PURPOSE

Active ingredients for NyQuil Sinus (in each LiquiCap) | Purpose
Acetaminophen 325 mg | Pain reliever
Doxylamine succinate 6.25 mg | Antihistamine
Phenylephrine HCl 5 mg | Nasal decongestant

Uses

temporarily relieves nasal and sinus symptoms:

- sinus pain
- headache
- nasal and sinus congestion
- runny nose and sneezing (NyQuil Sinus only)

Warnings

Liver warning: This product contains acetaminophen. Severe liver damage may occur if you take:

- more than 6 doses in 24 hours
- with other drugs containing acetaminophen
- 3 or more alcoholic drinks every day while using this product

Do not use

- with any other drug containing acetaminophen (prescription or nonprescription). Ask a doctor or pharmacist before using with other drugs if you are not sure
- if you are now taking a prescription monoamine oxidase inhibitor (MAOI) (certain drugs for depression, psychiatric or emotional conditions, or Parkison's disease), or for 2 weeks after stopping the MAOI drug. If you do not know if your prescription drug contains an MAOI, ask a doctor or pharmacist before taking this product.
- to make a child sleep

Ask a doctor before use if you have

- liver disease
- heart disease
- thyroid disease
- diabetes
- high blood pressure
- trouble urinating due to enlarged prostate gland
- a breathing problem such as emphysema or chronic bronchitis
- glaucoma

Ask a doctor or pharmacist before use if you are taking sedatives or tranquilizers.

When using these products

- do not use more than directed

In addition, when using NyQuil Sinus:

- excitability may occur, especially in children
- marked drowsiness may occur
- avoid alcoholic drinks
- be careful when driving a motor vehicle or operating machinery
- alcohol, sedatives, and tranquilizers may increase drowsiness

Stop use and ask a doctor if

- redness or swelling is present
- symptoms do not get better within 7 days or are accompanied by a fever
- you get nervous, dizzy or sleepless
- fever gets worse or lasts more than 3 days
- new symptoms occur

PREGNANCY OR BREAST FEEDING

If pregnant or breast-feeding, ask a health professional before use.

Keep out of reach of children.

Overdose warning: Taking more than the recommended dose can cause serious health problems. In case of overdose, get medical help or contact a Poison Control Center right away. Quick medical attention is critical for adults as well as for children even if you do not notice any signs or symptoms.

Directions

- take only as recommended - see Overdose warning
- do not exceed 6 doses per 24 hours

NyQuil Sinus OR DayQuil Sinus

adults and children 12 years and over | 2 LiquiCaps with water every 4 hours
children 2 to under 12 years | ask a doctor
children under 2 years | do not use

- when using other DayQuil or NyQuil products, carefully read each label to insure correct dosing

Other information

- store at room temperature

Inactive ingredients

NyQuil Sinus FD&C Blue No. 1, gelatin, glycerin, polyethylene glycol, povidone, propylene glycol, purified water, sorbitol special, titanium dioxide.

DayQuil Sinus FD&C Yellow No. 6, gelatin, glycerin, polyethylene glycol, povidone, propylene glycol, purified water, sorbitol special, titanium dioxide.

PRINCIPAL DISPLAY PANEL - 6000 Softgel Label

N-Time Sinus Soft Gelatin Capsules

Each Softgel Contains:
Acetaminophen USP 325mg
Doxylamine Succinate USP 6.25mg
Phenylephrine HCL USP 5mg

LOT NO : | NDC NO : 68210-1480-6
MFG DATE : | QUANTITY : 6000 Softgels
EXP DATE : | GROSS WT. :

WARNING:
KEEP OUT OF REACH OF CHILDREN

STORE AT CONTROLLED ROOM TEMPERATURE OF 59° - 86°F (15° - 30°C)
PROTECT FROM LIGHT, MOISTURE AND FREEZING

THIS BULK SHIPMENT IS INTENDED FOR FURTHER PACKAGING PROCESS ONLY.
CONTENTS SHOULD BE APPROVED, REPACKAGED IMMEDIATELY AND LABELED IN STRICT
CONFORMANCE WITH THE FD & C ACT AND REGULATIONS THEREUNDER.

MANUFACTURED BY:
Marksans Pharma Ltd
VERNA, GOA-403722,
INDIA.
CODE : GO/DRUGS/515

MANUFACTURED FOR:
SPIRIT PHARMACEUTICALS LLC
225 LINCOLN HWY, STE 205
FAIRLESS HILLS, PA 19030
PH.# 215 943 4000
FAX.# 215 943 4039

CAUTION : "FOR MANUFACTURING, PROCESSING OR REPACKING"